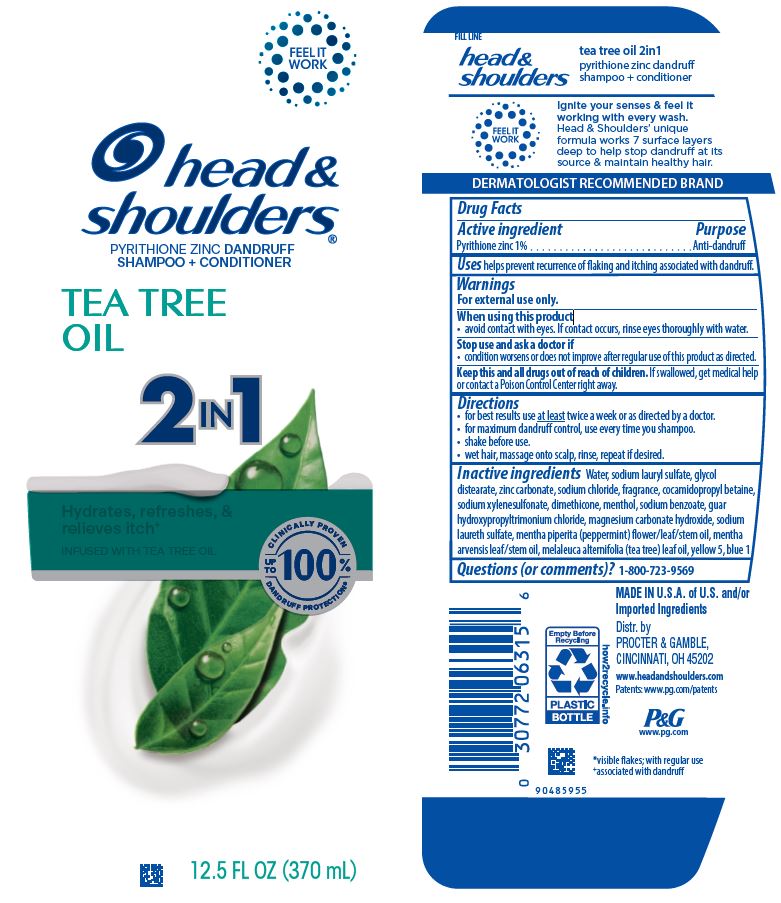 DRUG LABEL: Head and Shoulders Tea Tree Oil 2in1
NDC: 69423-417 | Form: LOTION/SHAMPOO
Manufacturer: The Procter & Gamble Manufacturing Company
Category: otc | Type: HUMAN OTC DRUG LABEL
Date: 20260218

ACTIVE INGREDIENTS: PYRITHIONE ZINC 1 g/100 mL
INACTIVE INGREDIENTS: MENTHA ARVENSIS LEAF OIL; TEA TREE OIL; FD&C YELLOW NO. 5; GLYCOL DISTEARATE; WATER; SODIUM LAURYL SULFATE; SODIUM LAURETH-3 SULFATE; ZINC CARBONATE; SODIUM CHLORIDE; SODIUM XYLENESULFONATE; DIMETHICONE; COCAMIDOPROPYL BETAINE; SODIUM BENZOATE; GUAR HYDROXYPROPYLTRIMONIUM CHLORIDE (1.7 SUBSTITUENTS PER SACCHARIDE); MAGNESIUM CARBONATE HYDROXIDE; FD&C BLUE NO. 1; MENTHOL, UNSPECIFIED FORM; PEPPERMINT OIL

Head and Shoulders® Tea Tree Oil 2in1
Men Old Spice ® Pure Sport

Drug Facts

Active ingredient

Pyrithione zinc 1%

Purpose

Anti-dandruff

Uses

helps prevent recurrence of flaking and itching associated with dandruff.

Warnings

For external use only.

When using this product

- avoid contact with eyes. If contact occurs, rinse eyes thoroughly with water.

Stop use and ask a doctor if

- condition worsens or does not improve after regular use of this product as directed.

KEEP OUT OF REACH OF CHILDREN

Keep this and all drugs out of reach of children. If swallowed, get medical help or contact a Poison Control Center right away.

Directions

- for best results use at least twice a week or as directed by a doctor.
- for maximum dandruff control, use every time you shampoo.
- shake before use.
- wet hair, massage onto scalp, rinse, repeat if desired.

Inactive ingredients

Water, sodium lauryl sulfate, glycol distearate, zinc carbonate, sodium chloride, fragrance, cocamidopropyl betaine, sodium xylenesulfonate, dimethicone, menthol, sodium benzoate, guar hydroxypropyltrimonium chloride, magnesium carbonate hydroxide, sodium laureth sulfate, mentha piperita (peppermint) flower/leaf/stem oil, mentha arvensis leaf/stem oil, melaleuca alternifolia (tea tree) leaf oil, yellow 5, blue 1

Questions (or comments)?

1-800-723-9569

Dist. by PROCTER & GAMBLE,
CINCINNATI, OH 45202

PRINCIPAL DISPLAY PANEL - 370 mL Bottle Label

head &
shoulders ®

pyrithione zinc dandruff

shampoo + conditioner

TEA TREE
OIL

2in1

12.5 FL OZ (370 mL)